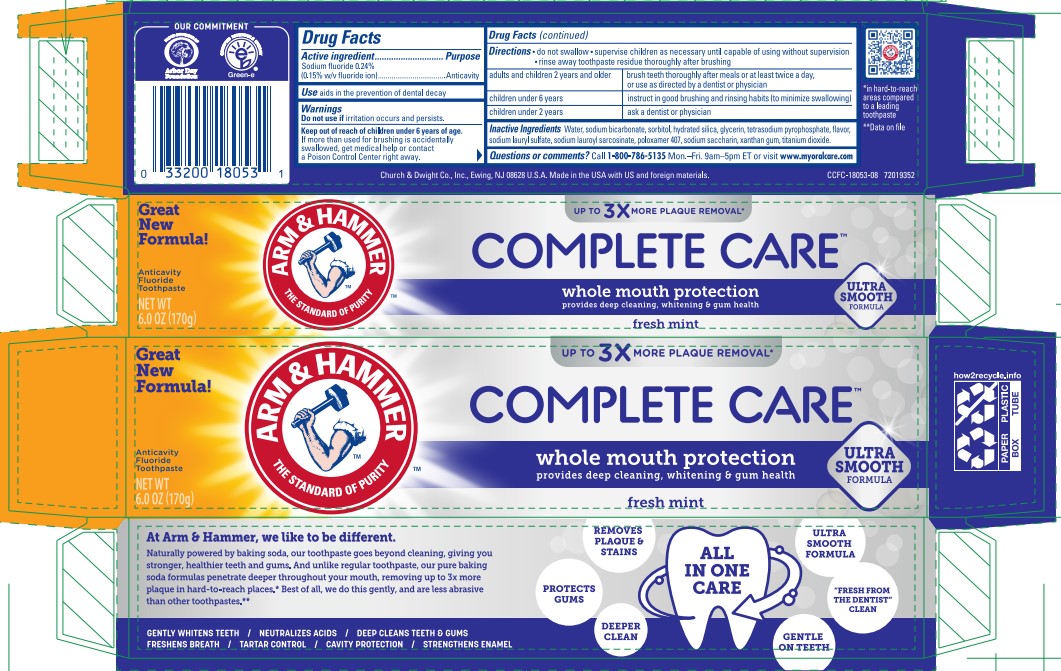 DRUG LABEL: Complete Care Whole Mouth Protection
NDC: 10237-675 | Form: PASTE, DENTIFRICE
Manufacturer: Church & Dwight Co., Inc.
Category: otc | Type: HUMAN OTC DRUG LABEL
Date: 20250909

ACTIVE INGREDIENTS: SODIUM FLUORIDE 1.5 mg/1 g
INACTIVE INGREDIENTS: POLYETHYLENE GLYCOL 400; SODIUM BICARBONATE; WATER; SACCHARIN SODIUM; SODIUM PYROPHOSPHATE; SODIUM LAURYL SULFATE; SODIUM LAUROYL SARCOSINATE; HYDRATED SILICA; XANTHAN GUM; TITANIUM DIOXIDE; SORBITOL; GLYCERIN

Arm & Hammer Complete Care Whole Mouth Protection Fluoride Toothpaste

ACTIVE INGREDIENT

Sodium fluoride 0.24%

(0.15% w/v fluoride ion)

PURPOSE

Anticavity toothpaste

INDICATIONS AND USAGE

aids in the prevention of dental decay

Warnings
Do not use if irritation occurs and persists.

Do not useif irritation occurs and persists.

Keep out of reach of children under 6 years of age.
If more than used for brushing is accidentally swallowed, get medical help or contact a Poison Control Center right away.

Directions

Directionsdo not swallow • supervise children as necessary until capable of using without supervision • rinse away toothpaste residue throughly after brushing

adults and children 2 years and older | brush teeth thoroughly after meals or at least twice a day, or use as directed by a dentist or physician
children under 6 years | instruct in good brushing and rinsing habits (to minimize swallowing)
children under 2 years | ask a dentist or physician

INACTIVE INGREDIENT

Water, sodium bicarbonate, sorbitol, hydrated silica, glycerin, tetrasodium pyrophosphate, flavor, sodium lauryl sulfate, sodium lauroyl sarcosinate, poloxamer 407, sodium saccharin, xanthan gum, titanium dioxide

Questions or comments?Call 1-800-786-5135Mon.-Fri. 9am-5pm ET or visit www.myoralcare.com

Principal Display Panel

Great

New

Formula!

Anticavity

Fluoride

Toothpaste

ARM AND HAMMER The Standard of Purity
UP TO 3X MORE PLAQUE REMOVAL*

COMPLETE CARE™

whole mouth protection

provides deep cleaning, whitening & gum health

fresh mint

ULTRA

SMOOTH

FORMULA

NET WT. 6.0 OZ. (170g)